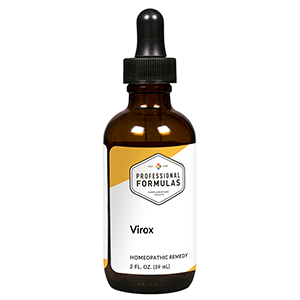 DRUG LABEL: Virox
NDC: 63083-6022 | Form: LIQUID
Manufacturer: Professional Complementary Health Formulas
Category: homeopathic | Type: HUMAN OTC DRUG LABEL
Date: 20190815

ACTIVE INGREDIENTS: CINCHONA OFFICINALIS BARK 3 [hp_X]/59 mL; NUTMEG 3 [hp_X]/59 mL; GELSEMIUM SEMPERVIRENS ROOT 6 [hp_X]/59 mL; PULSATILLA MONTANA WHOLE 6 [hp_X]/59 mL; SEPIA OFFICINALIS JUICE 6 [hp_X]/59 mL; CROTALUS HORRIDUS HORRIDUS VENOM 8 [hp_X]/59 mL; LACHESIS MUTA VENOM 8 [hp_X]/59 mL
INACTIVE INGREDIENTS: ALCOHOL; WATER

X22

ACTIVE INGREDIENTS

Cinchona officinalis 3X
Nux moschata 3X
Gelsemium sempervirens 6X
Pulsatilla 6X
Sepia 6X
Crotalus horridus 8X
Lachesis mutus 8X

QUESTIONS

Professional Formulas

PO Box 2034 Lake Oswego, OR 97035

INDICATIONS

For the temporary relief of runny nose, sneezing, cough, congestion, occasional headache, chills, sweats, sore throat, minor joint or muscle aches or pains, or exhaustion.*

PURPOSE

*Claims based on traditional homeopathic practice, not accepted medical evidence. Not FDA evaluated.

WARNINGS

Persistent symptoms may be a sign of a serious condition. If symptoms persist or are accompanied by a fever, rash, or persistent headache, consult a doctor. Keep out of the reach of children. In case of overdose, get medical help or contact a poison control center right away. If pregnant or breastfeeding, ask a healthcare professional before use.

Keep out of the reach of children.

PREGNANCY OR BREAST FEEDING

If pregnant or breastfeeding, ask a healthcare professional before use.

DIRECTIONS

Place drops under tongue 30 minutes before/after meals. Adults and children 12 years and over: Take 10 drops up to 3 times per day. Consult a physician for use in children under 12 years of age.

OTHER INFORMATION

Tamper resistant. If seal is broken, do not use. After opening, close container tightly and store at room temperature away from heat.

INACTIVE INGREDIENTS

20% ethanol, purified water.

LABEL

Est 1985

Professional Formulas

Complementary Health

Virox

Homeopathic Remedy

2 FL. OZ. (59 mL)